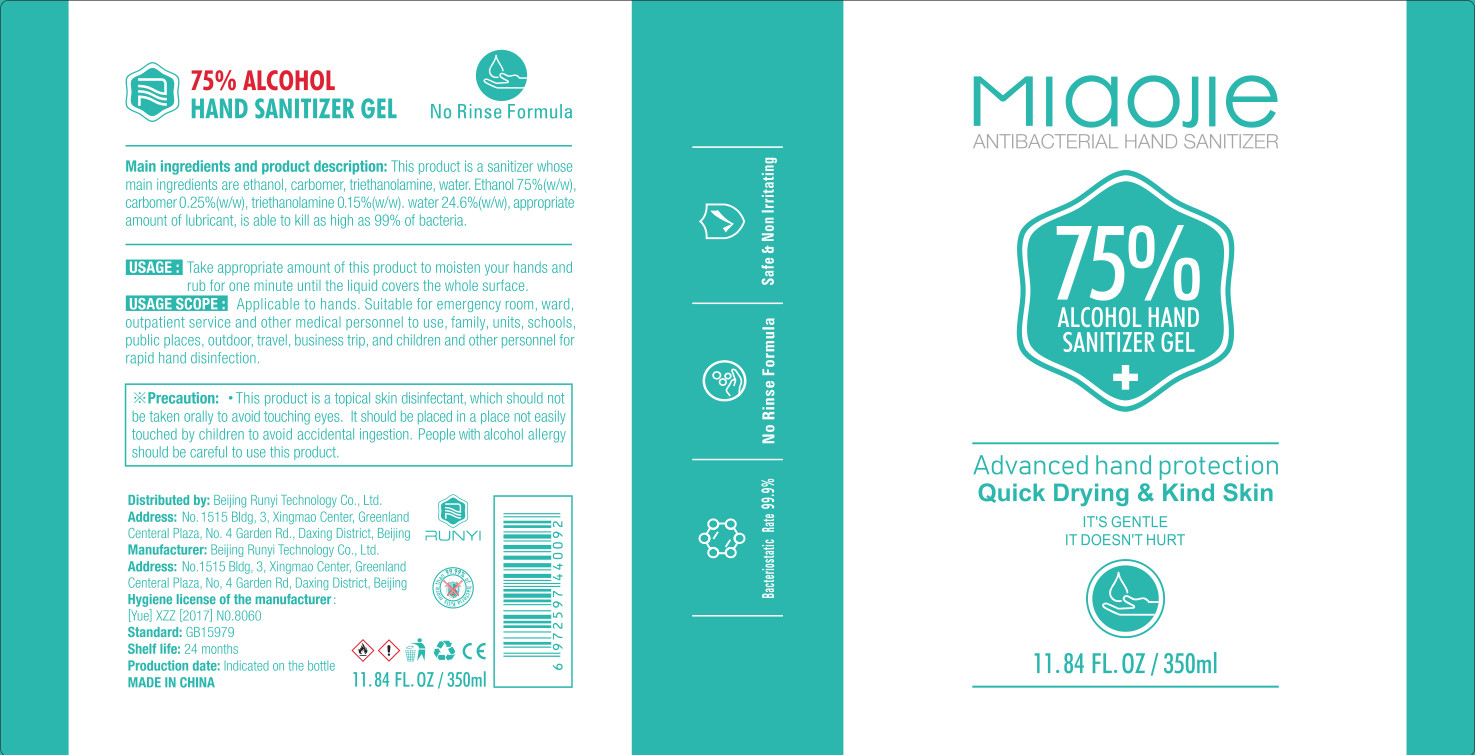 DRUG LABEL: RUNYI MIAOJIE Hand sanitizer
NDC: 41500-007 | Form: GEL
Manufacturer: Beijing Runyi Technology Co., Ltd
Category: otc | Type: HUMAN OTC DRUG LABEL
Date: 20200507

ACTIVE INGREDIENTS: ALCOHOL 262.5 mL/350 mL; CARBOMER HOMOPOLYMER, UNSPECIFIED TYPE 0.875 g/350 mL; TROLAMINE 0.525 g/350 mL
INACTIVE INGREDIENTS: WATER

DOSAGE AND ADMINISTRATION

Don't put it in a dry place

INACTIVE INGREDIENT

water

INDICATIONS AND USAGE

Take appropriate amount of this product to moisten your hands and rub for one minute until the liquid covers the whole surface.

ACTIVE INGREDIENT

carbomer

triethanolamine

ethanol

keep out of reach of children

PURPOSE

Disinfection
Sterilization
No Rinseing

WARNINGS

This product is a topical skin disinfectant, which should not be taken orally to avoid touching eyes. It should be placed in a place not easily touched by children to avoid accidental ingestion. People with alcohol allergy should be careful to use this product.